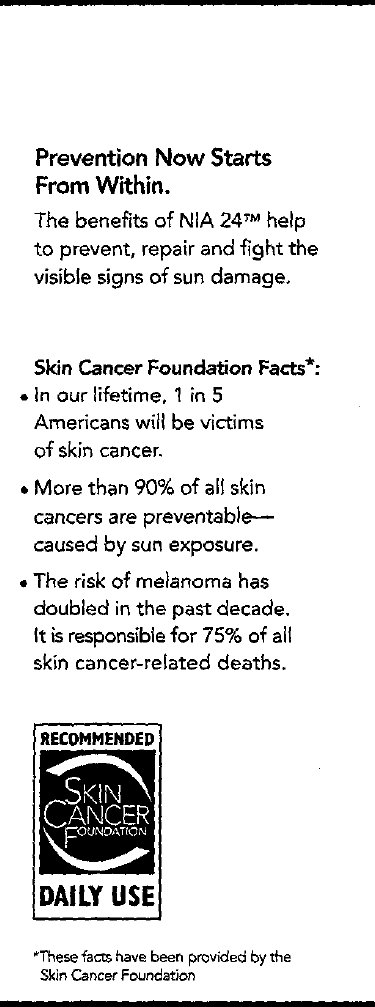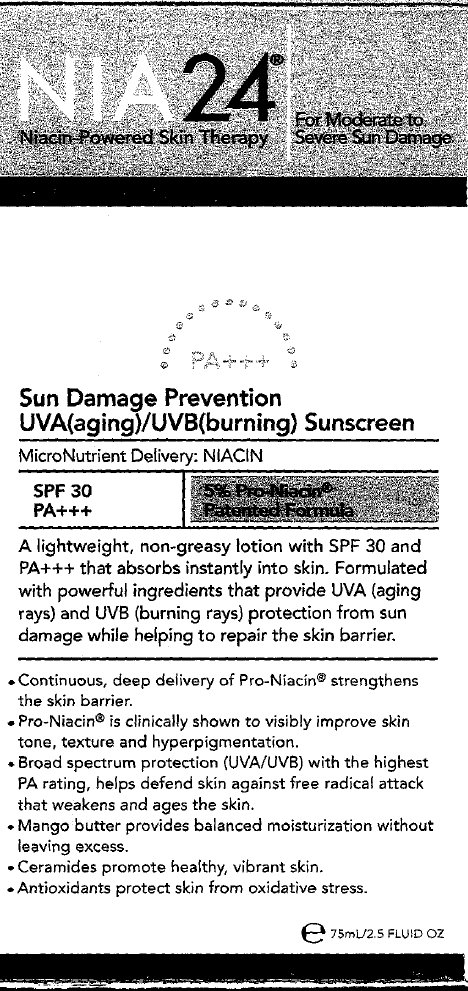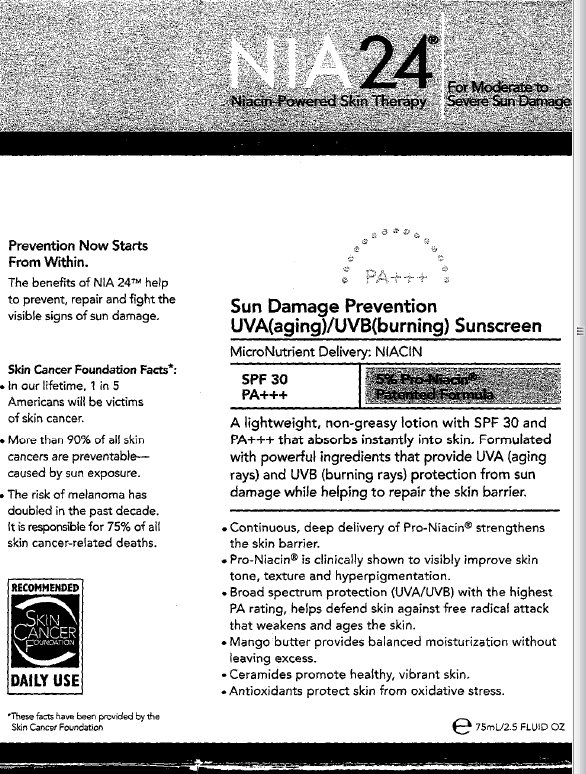 DRUG LABEL: NIA 24  SPF 30
NDC: 43115-123 | Form: LOTION
Manufacturer: Niadyne Inc
Category: otc | Type: HUMAN OTC DRUG LABEL
Date: 20250207

ACTIVE INGREDIENTS: HOMOSALATE 75 mg/1 mL; OCTISALATE 50 mg/1 mL; AVOBENZONE 30 mg/1 mL; OCTOCRYLENE 26 mg/1 mL
INACTIVE INGREDIENTS: WATER; DIPROPYLENE GLYCOL; MYRISTYL NICOTINATE; POLYESTER-8 (1400 MW, CYANODIPHENYLPROPENOYL CAPPED); CYCLOMETHICONE; GLYCERYL MONOSTEARATE; PANTHENOL; POTASSIUM CETYL PHOSPHATE; BUTYLENE GLYCOL; MANGIFERA INDICA SEED BUTTER; HYDROGENATED PALM GLYCERIDES; GLYCYRRHIZINATE DIPOTASSIUM; SOYBEAN; CERAMIDE 2; CERAMIDE 3; LYCIUM CHINENSE FRUIT; LOWBUSH BLUEBERRY; ARCTOSTAPHYLOS UVA-URSI LEAF; PEG-100 STEARATE; SODIUM POLYACRYLATE (2500000 MW); ISOHEXADECANE; SORBITAN SESQUIOLEATE; POLYSORBATE 80; CETYL ALCOHOL; XANTHAN GUM; CARBOMER INTERPOLYMER TYPE A (ALLYL SUCROSE CROSSLINKED); POTASSIUM HYDROXIDE; EDETATE DISODIUM; PHENOXYETHANOL; CAPRYLYL GLYCOL; NUTMEG

NIA 24 SPF 30

ACTIVE INGREDIENT

Active Ingredients Purpose Homosalate 7.5%.................................Sunscreen Octisalate 5.0%...................................Sunscreen Avobenzone 3.0%................................Sunscreen Octocrylene 2.6%................................Sunscreen

PURPOSE

Uses - for prevention of sunburn

Warnings For external use only.

When using this product, keep out of eyes. Rinse with water to remove.

Stop use and ask a doctor if rash or irritation develops and lasts.

ASK DOCTOR

For children 6 months of age or under , consult a doctor prior to use.

Keep out of reach of children.

INDICATIONS AND USAGE

If swallowed, get medical help or contact a poison control center right away.

PRECAUTIONS

UV exposure from the sun increases the risk of skin cancer, premature skin aging, and other skin damage. It is important to decrease UV exposure by limiting time in the sun, wearing protective clothing, and using a sunscreen.

DOSAGE AND ADMINISTRATION

Directions - Apply a dime sized amount in the morning on cleansed face and neck or over a moisturizer. - Reapply as needed or after towel drying, swimming or perspiring.

INACTIVE INGREDIENT

Inactive Ingredients Water (Aqua/Eau), Dipropylene Glycol, Myristyl Nicotinate, Polyester-8, Caprylyl Methicone, Cyclomethicone, Glyceryl Stearate, Polyacrylate-15, Panthenol, Potassium Cetyl Phosphate, Butylene Glycol, Mangifera Indica (Mango) Seed Butter, Methyl Glucose Sesquistearate, Hydrogenated Palm Glycerides, Polyacrylate-17, Dipotassium Glycyrrhizate, Glycine Soja (Soybean) Seed Extract, Ceramide 2, Ceramide 3, Lycium Chinensis Fruit Extract, Vaccinium Angustifolium (Blueberry) Fruit Extract, Arctostaphylos Uva Ursi Leaf Extract, PEG-100 Stearate, Sodium Acrylate/Sodium Acryloyldimethyl Taurate Copolymer, Isohexadecane, Sorbitan Sesquioleate, Polysorbate 80, Cetyl Alcohol, Tocopheryl Acetate, Xanthan Gum, Acrylates/C10-30 Alkyl Acrylate Crosspolymer, Potassium Hydroxide, Disodium EDTA, Phenoxyethanol, Caprylyl Glycol, Myristica Fragrans (Nutmeg) Kernel Extract.

DESCRIPTION

Prevention Now Starts From Within. The benefits of NIA 24TM help to prevent, repair and fight the visible signs of sun damage. Skin Cancer Foundation Facts*: - In our lifetime, 1 in 5 Americans will be victims of skin cancer. - More than 90% of all skin cancers are preventable--- caused by sun exposure. - The risk of melanoma has doubled in the past decade. It is responsible for 75% of all skin cancer-related deaths. *These facts have been provided by the Skin Cancer Foundation. - Improve the appearance of sun damage, hyperpigmentation and brown spots. - Reduce the appearance of fine lines and wrinkle. - Improve skin tone, texture and firmness. - See stronger skin with a better self-defense against visible signs of sun damage and moisture loss. Physician Recommended Allergy Tested Fragrace, Color and Dye Free Non-Comedogenic.

PACKAGE LABEL

NIA 24 Niacin-Powered Skin Therapy Sun Damage Prevention UVA/UVB Sunscreen Micro Nutrient Deliver: NIACHI SPF 30 PA +++ 5% Pro-Niacin Patented Formula For Moderate to Severs Sun Demage

PACKAGE LABEL

Active Ingredients: Homosalate (7.5%), Octisalate (5.0%), Avobenzone (3.0%), Octocrylene (2.6%). Uses - for prevention of sunburn Warnings For external use only.When using this product, keep out of eyes. Rinse with water to remove.Stop use and ask a doctor if rash or irritation develops and lasts.For children 6 months of age or under , consult a doctor prior to use.Keep out of reach of children.If swallowed, get medical help or contact a poison control center right away.UV exposure from the sun increases the risk of skin cancer, premature skin aging, and other skin damage. It is important to decrease UV exposure by limiting time in the sun, wearing protective clothing, and using a sunscreen. e 30mL/1 FLUID OZ. Covered by US Patents 6337065, 6552050, 6464992 NIADYNE, INC., Raieigh, NC 27609/BIORUS sprl, 2 rue Rene Descartes, B-7000 Mons, Belgium 866-NIADYNE (642-3963) www.NIA24.com Made in the USA 12M

PACKAGE LABEL

PreDamage PostDamage UnDamage NIA24 Niacin Powered Skin Therapy For Moderate Severe Sun Damage PA +++ Sun Damage Prevention UVA(aging)/UVB(burning) Sunscreen MicroNutrient Delivery: NIACIN SPF 30 PA+++ 5% Pro-Niacin Patented Formula A lightweight, non-greasy lotion with SPF 30 and PA+++ that absorbs instantly into skin. Formulated with powerful ingredients that provide UVA (aging rays) and UVB (burning rays) protection from sun damage while helping to repair the skin barrier. - Continuous, deep delivery of Pro-Niacin strengthens the skin barrier. - Pro-Niacin is clinically shown to visibly improve skin tone, texture and hyperpigmentation. - Broad spectrum protection (UVA/UVB) with the highest PA rating, helps defend skin against free radical attack that weakens and ages the skin. - Mango butter provides balanced moisturization without leaving excess. - Ceramides promote healthy, vibrant skin. - Antioxidants protect skin from oxidative stress. RECOMMENDED SKIN CANCER FOUNDATION DAILY USE * These facts have been provided by the Skin Cancer Foundation e 75mL/2.5 FLUID OZ 0141A1 EXP:01/2013 8 51203 00073 7

PACKAGE LABEL

Covered by US Patents 6337065, 6552050, 6464992 NIADYNE, INC., Raieigh, NC 27609/BIORUS sprl, 2 rue Rene Descartes, B-7000 Mons, Belgium For all consumer inquiries, please call 866-NIADYNE (642-3963) www.NIA24.com Made in the USA 12M NIA24 NIA24 NIA24 NIA24 NIA24 NIA24 NIA24 NIA24 NIA24